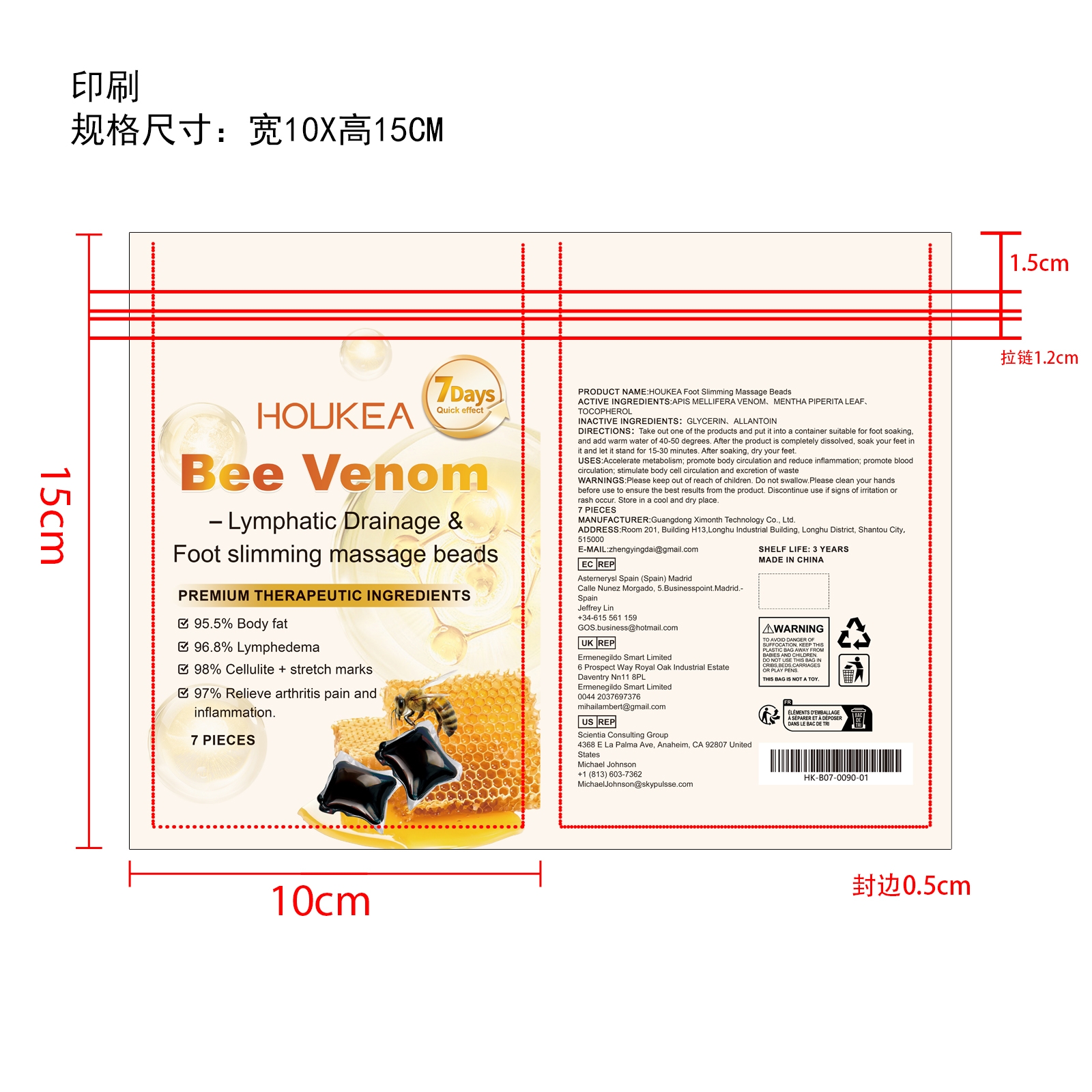 DRUG LABEL: HOUKEA Foot Slimming Massage Beads
NDC: 84660-093 | Form: LIQUID
Manufacturer: Guangdong Ximonth Technology Co., Ltd.
Category: otc | Type: HUMAN OTC DRUG LABEL
Date: 20241029

ACTIVE INGREDIENTS: APIS MELLIFERA VENOM 0.7 g/7 g; MENTHA PIPERITA LEAF 0.7 g/7 g; TOCOPHEROL 1.05 g/7 g
INACTIVE INGREDIENTS: GLYCERIN 1.05 g/7 g; ALLANTOIN 2.1 g/7 g

ACTIVE INGREDIENTS

APIS MELLIFERA VENOM、MENTHA PIPERITA LEAF、 TOCOPHEROL

PURPOSE

Accelerate metabolism; promote body circulation and reduce inflammation; promote blood circulation; stimulate body cell circulation and excretion of waste

USES

Take out one of the products and put it into a container suitable for foot soaking.and add warm water of 40-50 degrees. After the product is completely dissolved, soak your feet init and let it stand for 15-30 minutes. After soaking, dry your feet.

WARNINGS

Please keep out of reach of children. Do not swallow.Please clean your hands before use to ensure the best results from the product. Discontinue use if signs of irritation or rash occur. Store in a cool and dry place.

STOP USE

Discontinue use if signs of irritation or rash occur.

DO NOT USE

Discontinue use if signs of irritation or rash occur.

KEEP OUT OF REACH OF CHILDREN

Please keep out of reach of children. Do not swallow.

STORAGE AND HANDLING

Store in a cool and dry place.

INACTIVE INGREDIENT

GLYCERIN、ALLANTOIN